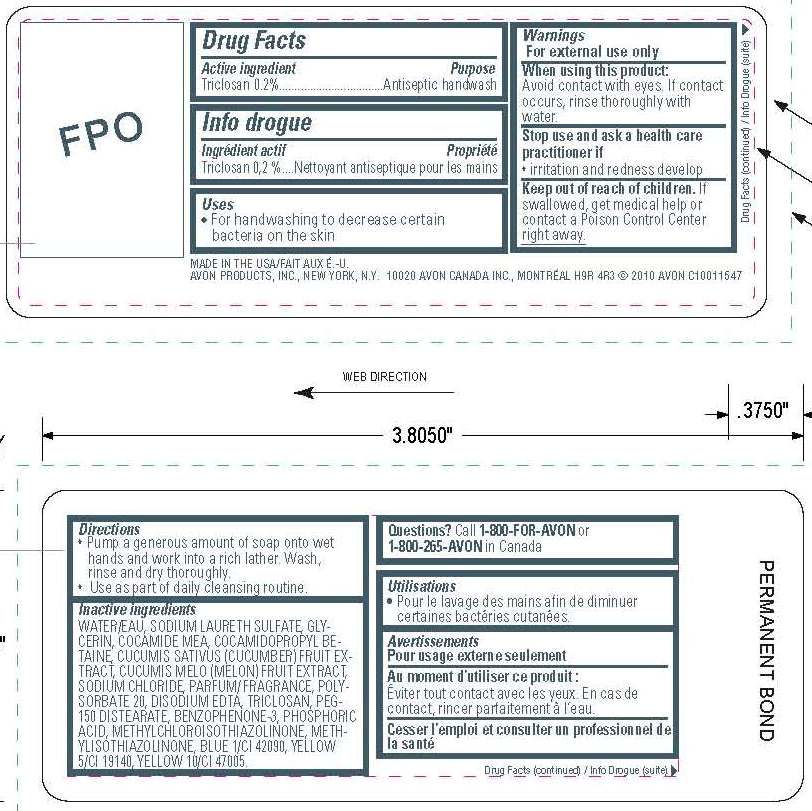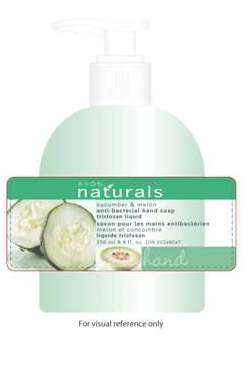 DRUG LABEL: Naturals Cucumber and Melon
NDC: 10096-0208 | Form: LIQUID
Manufacturer: New Avon LLC
Category: otc | Type: HUMAN OTC DRUG LABEL
Date: 20160212

ACTIVE INGREDIENTS: TRICLOSAN 2 mg/1 mL

Active ingredient

Triclosan 0.20%.................

Purpose

..................Antiseptic handwash

Uses

- for handwashing to decrease certain bacteria on the skin

Warnings
For external use only

When using this product:
Avoid contact with eyes. If contact occurs, rinse thoroughly with water.

Stop use and ask a healthcare practitioner if

- irritation and redness develop

Keep out of reach of children. If swallowed, get medical help or contact a poison control center right away.

Directions

- Pump a generous amount of soap onto wet hands and work into a rich lather. Wash, rinse and dry thoroughly.
- Use as part of daily cleansing routine.

Inactive Ingredients

WATER/EAU
SODIUM LAURETH SULFATE
GLYCERIN
COCAMIDE MEA
COCAMIDOPROPYL BETAINE
CUCUMIS SATIVUS (CUCUMBER) FRUIT EXTRACT
CUCUMIS MELO (MELON) FRUIT EXTRACT
SODIUM CHLORIDE
PARFUM/FRAGRANCE
POLYSORBATE 20
DISODIUM EDTA
PEG-150 DISTEARATE
BENZOPHENONE-3
PHOSPHORIC ACID
METHYLCHLOROISOTHIAZOLINONE
METHYLISOTHIAZOLINONE
BLUE 1/CI 42090
YELLOW 5/CI 19140
YELLOW 10/CI 47005

QUESTIONS

Questions? Call 1-800-FOR-AVON or 1-800-265-AVON in Canada